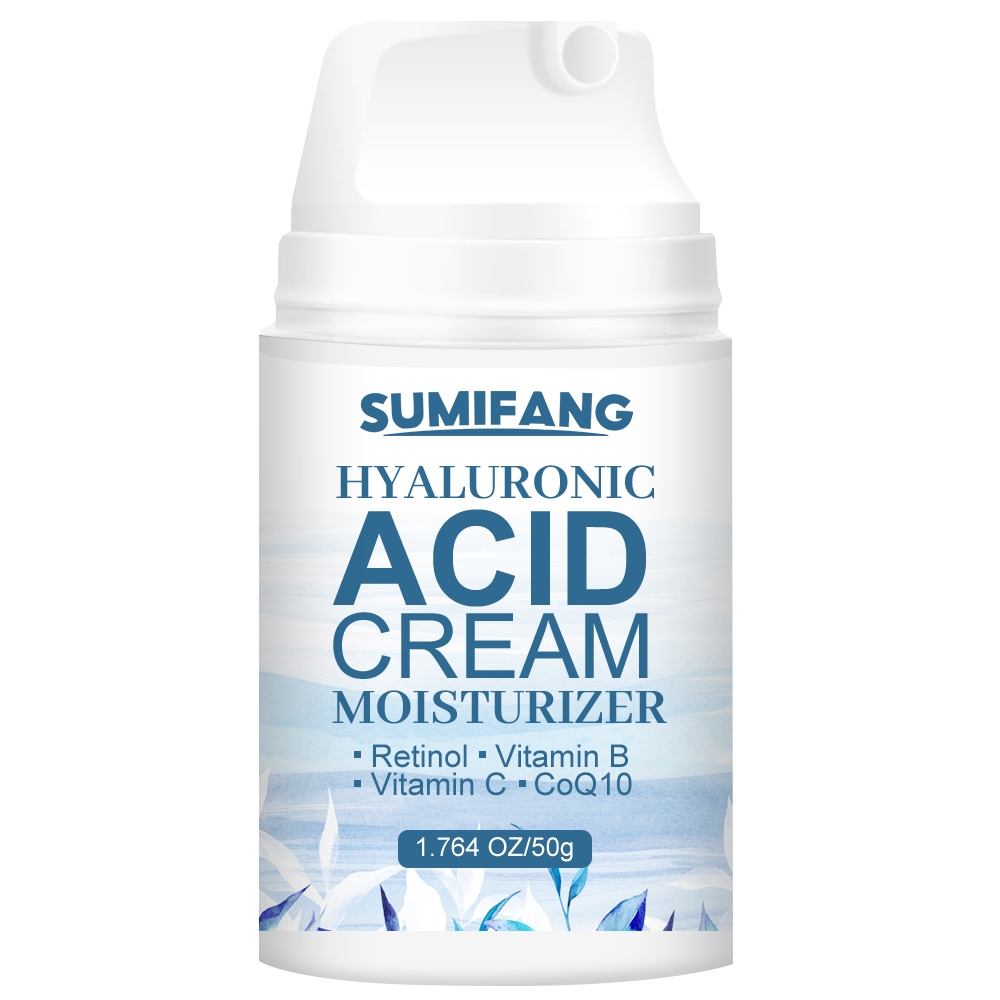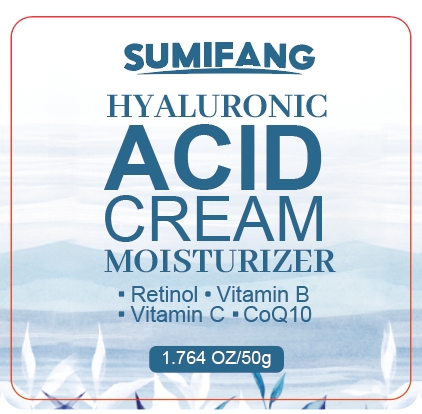 DRUG LABEL: ACIDCREAM
NDC: 84025-146 | Form: CREAM
Manufacturer: Guangzhou Yanxi Biotechnology Co.. Ltd
Category: otc | Type: HUMAN OTC DRUG LABEL
Date: 20240814

ACTIVE INGREDIENTS: GLYCERIN 3 mg/40 g; HYALURONIC ACID 5 mg/40 g
INACTIVE INGREDIENTS: WATER

DOSAGE AND ADMINISTRATION

For moisturizing and whitening skin

WARNINGS

Keep out of children

INACTIVE INGREDIENT

Aqua

INDICATIONS AND USAGE

For daily skin care

Keep out of children

PURPOSE

Replenishes moisture for the skin and relieves dry skin discomfort